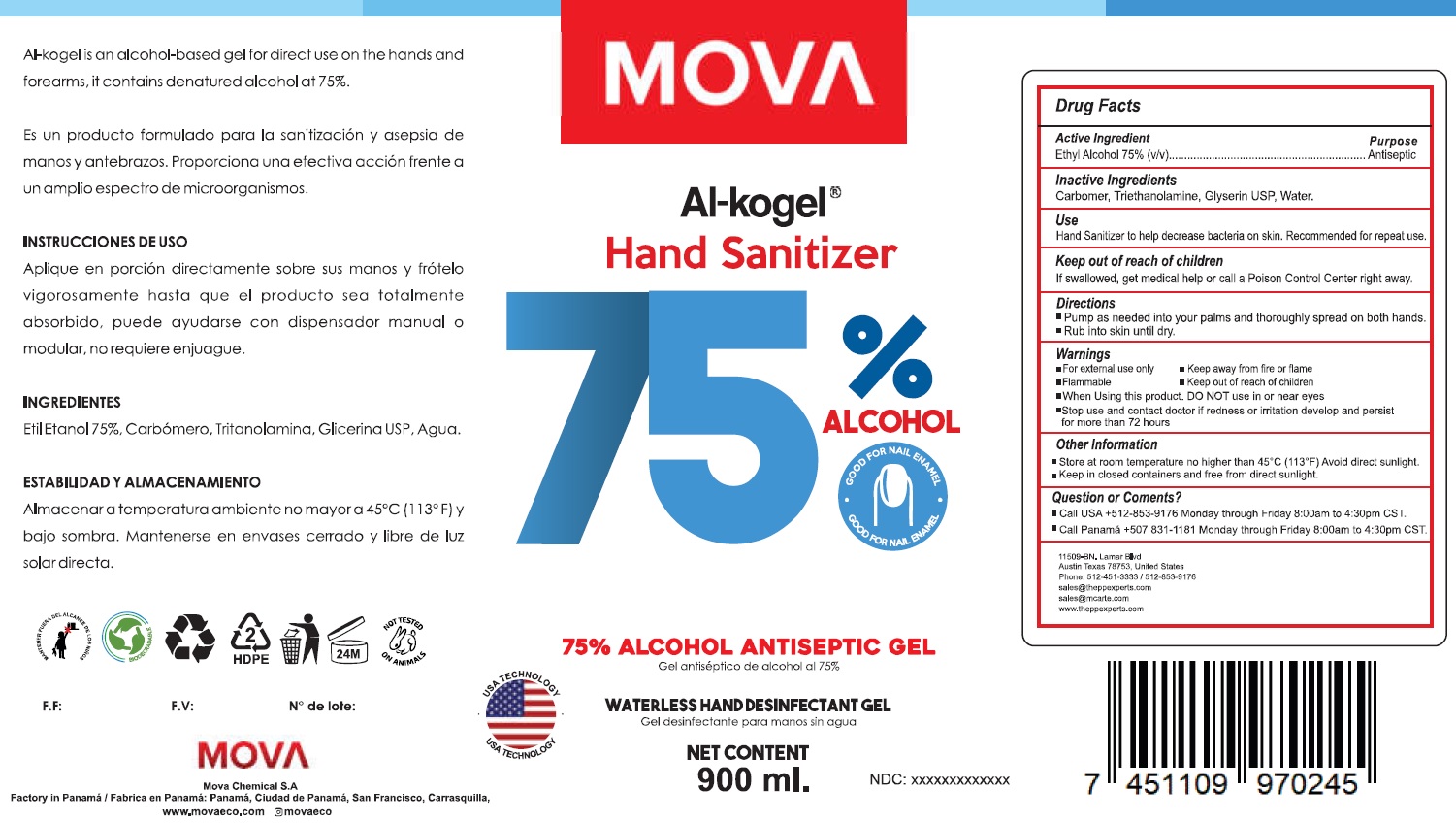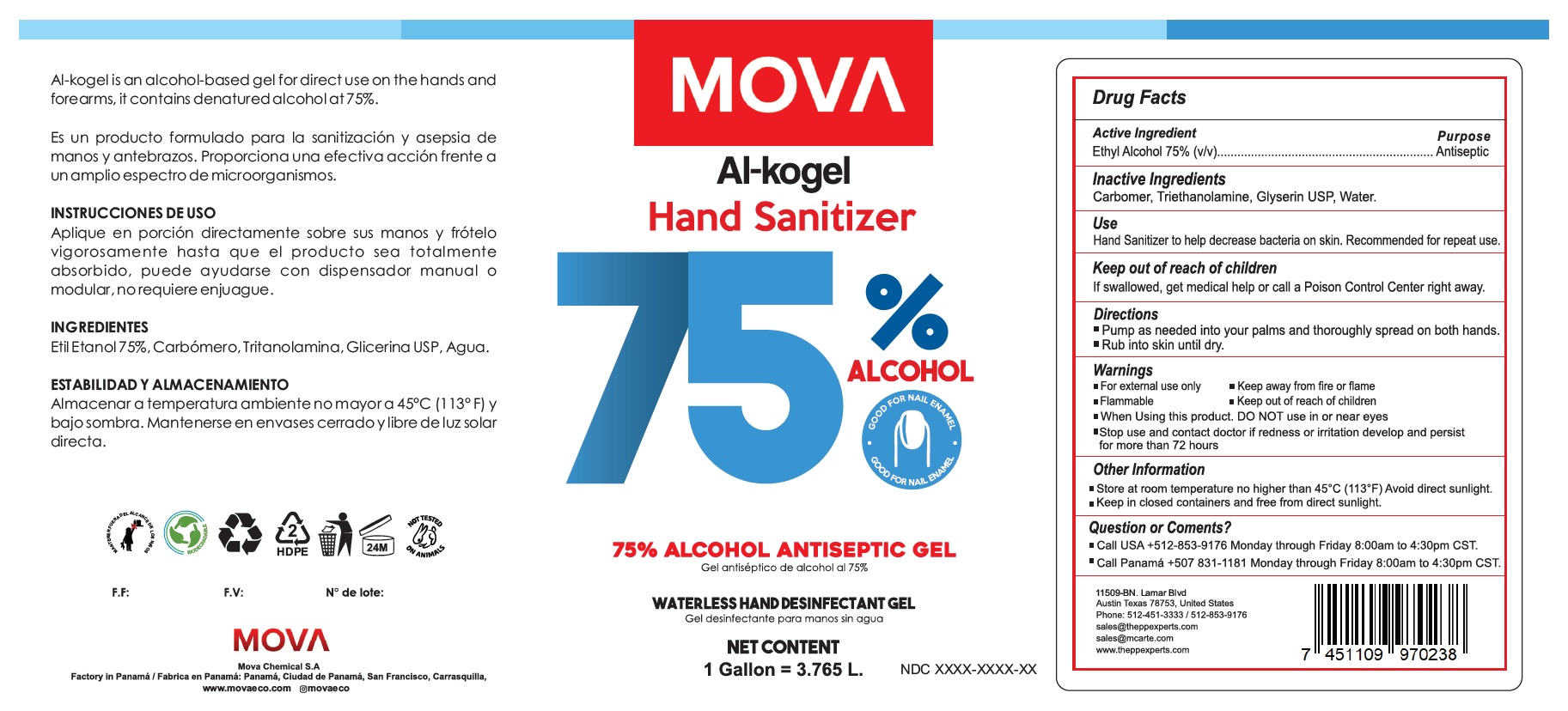 DRUG LABEL: Mova al-kogel hand sanitizer 75 Alcohol
NDC: 81235-003 | Form: LIQUID
Manufacturer: Mova Chemical S.A
Category: otc | Type: HUMAN OTC DRUG LABEL
Date: 20230104

ACTIVE INGREDIENTS: ALCOHOL 0.75 mL/1 mL
INACTIVE INGREDIENTS: CARBOMER HOMOPOLYMER, UNSPECIFIED TYPE; TROLAMINE; GLYCERIN; WATER

Mova al-kogel hand sanitizer 75% Alcohol

Active Ingredient

Ethyl Alcohol 75% (v/v)

Purpose

Antiseptic

Inactive Ingredients

Carbomer, Triethanolamine, Glyserin USP, Water.

Use

Hand Sanitizer to help decrease bacteria on skin. Recommended for repeat use.

Directions

- Pump as needed into your palms and thoroughly spread on both hands.
- Rub into skin until dry.

Warnings

- For external use only
- Flammable
- Keep away from fire or flame

Keep out of reach of children

If swallowed, get medical help or call a Poison Control Center right away.

DO NOT use

in or near eyes

Stop use and contact doctor

- if redness or irritation develop and persist for more than 72 hours

Other Information

- Store at room temperature on higher than 45°C (113°F) Avoid direct sunlight.
- Keep in closed containers and free from direct sunlight.

Question or Coments?

- Call USA +512-853-9176 Monday through Friday 8:00am to 4:30pm CST.
- Call Panama +507 831-1181 Monday through Friday 8:00am to 4:30pm CST.